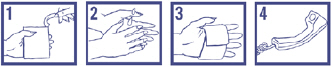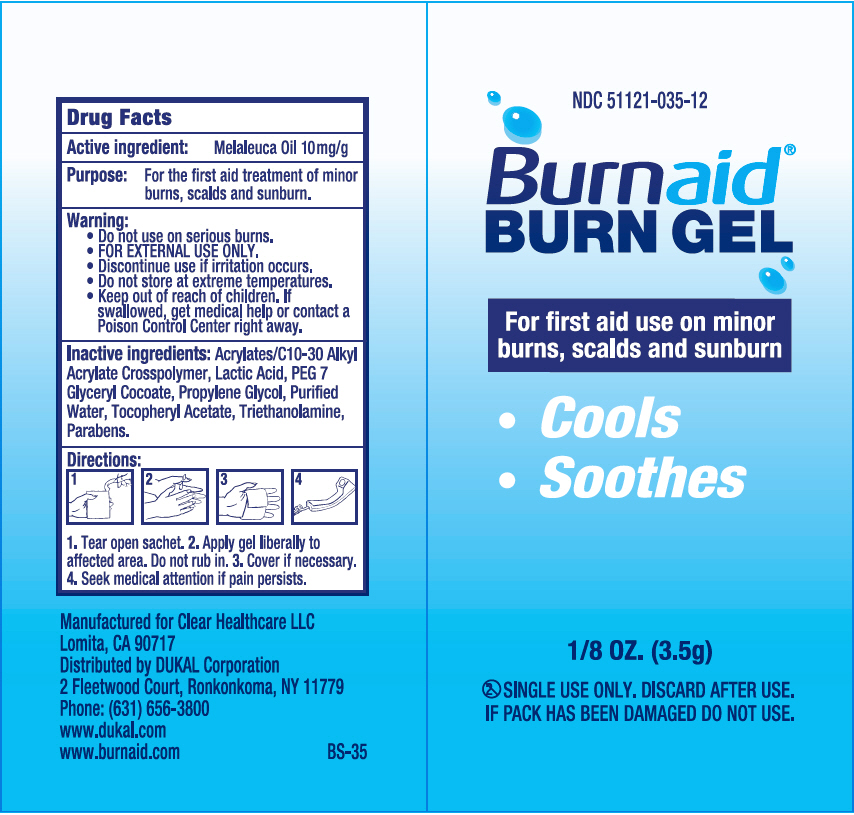 DRUG LABEL: Burnaid Burn Gel
NDC: 51121-035 | Form: GEL
Manufacturer: Clear Healthcare LLC
Category: otc | Type: HUMAN OTC DRUG LABEL
Date: 20140319

ACTIVE INGREDIENTS: Tea Tree Oil 10 mg/1 g
INACTIVE INGREDIENTS: Water; Propylene Glycol; PEG-7 Glyceryl Cocoate; Trolamine; .Alpha.-Tocopherol Acetate; Lactic Acid

Burnaid® Burn Gel

Drug Facts

Active ingredient

Meleleuca Oil 10mg/g

PURPOSE

Purpose

For the first aid treatment of minor burns, scalds and sunburn.

Warning

- Do not use on serious burns.

WHEN USING

- FOR EXTERNAL USE ONLY.

- Discontinue use if irritation occurs.

- Do not store at extreme temperatures.

- Keep out of reach of children. If
- swallowed, get medical help or contact a Poison Control Center right away.

Inactive ingredients

Purified Water, Propylene Glycol, PEG 7 Glyceryl Cocoate, Acrylates/C10-30 Alkyl Acrylate Crosspolymer, Triethanolamine, Tocopheryl Acetate, Lactic Acid, Parabens

Directions

1. Tear open sachet. 2. Apply gel liberally to affected area. Do not rub in. 3. Cover if necessary.

4. Seek medical attention if pain persists.

PRINCIPAL DISPLAY PANEL - 3.5 g Packet Label

NDC 51121-035-12

Burnaid®
BURN GEL

For first aid use on minor
burns, scalds and sunburn

- Cools
- Soothes

1/8 OZ. (3.5g)

SINGLE USE ONLY. DISCARD AFTER USE.
IF PACK HAS BEEN DAMAGED DO NOT USE.